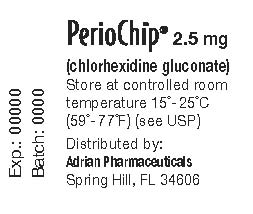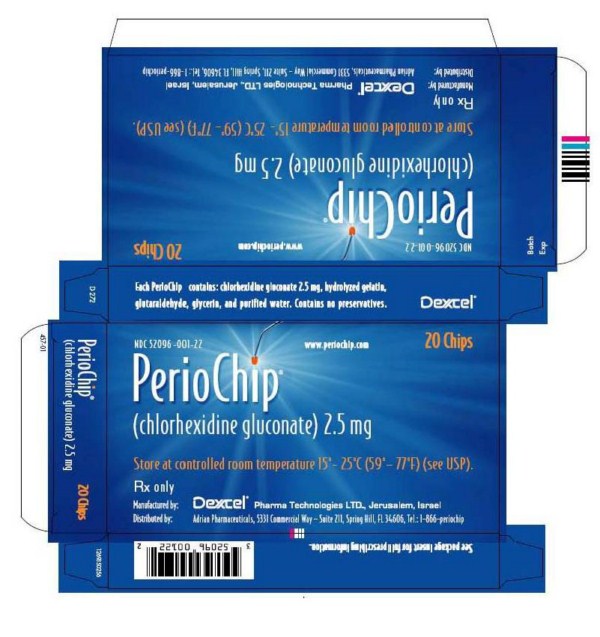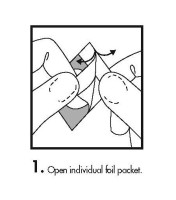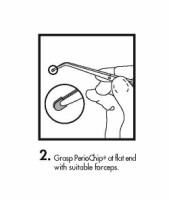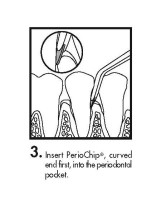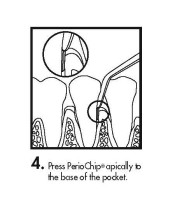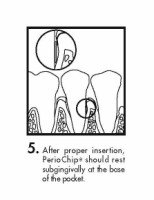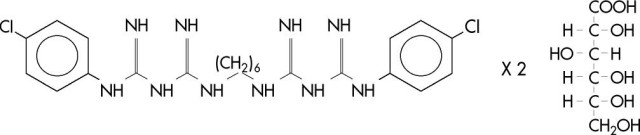 DRUG LABEL: PerioChip
NDC: 52096-001 | Form: INSERT, EXTENDED RELEASE
Manufacturer: Adrian Pharmaceuticals, LLC
Category: prescription | Type: HUMAN PRESCRIPTION DRUG LABEL
Date: 20100305

ACTIVE INGREDIENTS: Chlorhexidine Gluconate 2.5 mg/1 1
INACTIVE INGREDIENTS: Gelatin; Glutaral; Glycerin; Water

PerioChip, 2.5 mg (Chlorhexidine Gluconate)

DESCRIPTION

PerioChip® (chlorhexidine gluconate) is a small, orange-brown, rectangular chip (rounded at one end) for insertion into periodontal pockets. Each PerioChip weighs approximately 7.4 mg and contains 2.5 mg of chlorhexidine gluconate in a biodegradable matrix of hydrolyzed gelatin (cross-linked with glutaraldehyde). PerioChip also contains glycerin and purified water.
Chlorhexidine gluconate is an antimicrobial agent. Chemically, it is designated as 1,1’-hexamethylenebis [5-(p-chlorophenyl)biguanide] di-D-gluconate, and its molecular formula is C22H30Cl2N10.2C6H12O7. The molecular weight is 897.8. The structural formula of chlorhexidine gluconate is:

Microbiology

Chlorhexidine gluconate is active against a broad spectrum of microbes. The chlorhexidine molecule, due to its positive charge, reacts with the microbial cell surface, destroys the integrity of the cell membrane, penetrates into the cell, precipiates the cytoplasm, and the cell dies. Studies with PerioChip showed reductions in the numbers of the putative periodontopathic organisms Porphyromonas (Bacteroides) gingivalis, Prevotella (Bacteroides) intermedia, Bacteroides forsythus, and Campylobacter rectus (Wolinella recta) after placement of the chip. No overgrowth of opportunistic organisms or the adverse changes in the oral microbial ecosystem were noted. The relationship of the microbial findings to clinical outcome has not been established.

Pharmacokinetics

PerioChip releases chlorhexidine in vitro in a biphasic manner, initially releasing approximately 40% of the chlorhexidine within the first 24 hours and then releasing the remaining chlorhexidine in an almost linear fashion for 7-10 days. This enzymatic release rate assay is an experimental collagenase assay that differs from the Regulatory Specification’s Agar Release Rate Assay. This release profile may be explained as an initial burst effect, dependent on diffusion of chlorhexidine from the chip, followed by a further release of chlorhexidine as a result of enzymatic degradation.

In an in vivo study of 18 evaluable adult patients, there were no detectable plasma or urine levels of chlorhexidine following the insertion of 4 PerioChips under clinical conditions. The concentration of chlorhexidine released from the PerioChip was determined in the gingival crevicular fluid (GCF) of these same subjects. In these subjects, a highly variable biphasic release profile for chlorhexidine was demonstrated, with GCF levels 4 hours after chip insertion (mean: 1444 ± 783 µg/mL), followed by a second peak at 72 hours (mean: 1902 ± 1073 µg/mL). In a second study involving the insertion of 1 PerioChip under clinical conditions, the mean GCF level of chlorhexidine peaked at 1088 ± 678 µg/mL at 4 hours. The mean GCF levels then declined in a highly erratic fashion to levels of 482 ± 447 µg/mL at 72 hours without producing a true second peak.

The results of these studies confirm a high degree of intersubject variability in chlorhexidine release from the PerioChip matrix in vivo that was not seen in vitro. Due to the nature and clinical use of the PerioChip dosage form, dose proportionality was not and would not be expected to be demonstrated between the two studies.

Clinical Studies

SIn two double-blind, randomized, controlled clinical trials, 447 adult patients with periodontitis were entered who had at least 4 pockets with probing depth of 5-8 mm that bled on probing. Patients studied were in good general health. Diabetics were excluded from the studies. PerioChip was not studied in acutely abscessed periodontal pockets. Patients were free of supragingival calculus prior to baseline. In these two studies, the effects of scaling and root planing (SRP) alone, and SRP followed by PerioChip treatment, were compared. All patients received full mouth SRP at baseline. If the pocket depth remained ≥ 5 mm at 3 and/or 6 months after initial treatment, another chip was placed into the pocket. Teeth treated with PerioChip were found to have significantly reduced probing pocket depth (PD) compared with those treated with SRP alone at 9 months after initial treatment, as shown in Table 1

Table 1
Probing pocket depth (PD) at baseline and reduction in PD at 9 months
from 2 five-center U.S.clinical trials (in mm, mean ± SE)
 | Study #94-002 | Study #94-002 | Study #94-003 | Study #94-003
Time | SRP alone | SRP + PerioChip | SRP alone | SRP + PerioChip
PD at Baseline | 5.69 ± 0.58 (n = 107) | 5.79 ± 0.61 (n = 108) | 5.56 ± 0.54 (n = 115) | 5.67 ± 0.56 (N = 117)
PD Reduction at 9 months | 0.78 ± 0.07 (n = 101) | 1.06 ± 0.07* (n = 101) | 0.52 ± 0.07 (n = 107) | 0.84 ± 0.08** (n = 110)

SE = standard error; SRP = Scaling and Root Planing
Significantly different from SRP alone: *(p = 0.006); **(p = 0.001)

PerioChip treatment resulted in a greater percentage of pockets and patients that showed an improvement in PD of 2 mm or more compared with SRP alone at 9 months, as shown in Table 2. The differences in improvement were statistically significant when analyzed on a per patient basis (p less than 0.005). PerioChip treatment maintained probing attachment level (PAL) compared with baseline or with SRP alone at 9 months. The effects of PerioChip on bleeding upon probing have not been established. In the two studies, there were no significant changes in plaque development or gingivitis. Smokers and non-smokers were enrolled in these studies; although non-smokers using PerioChip demonstrated significant improvement in PD, smokers demonstrated a trend towards improvement that did not reach statistical significance. This finding is consistent with the consensus that smoking is a risk factor in periodontal diseases.

Table 2
Number (percentage) of pockets and patients with an improvement
in PD ≥ 2 mm at 9 months from 2 five-center U.S. clinical trials
 | Study #94-002 | Study #94-002 | Study #94-003 | Study #94-003
 | SRP alone | SRP + PerioChip | SRP alone | SRP + PerioChip
Pockets | 21 / 202 (11%) | 44 / 202 (22%) | 12 / 214 (6%) | 36 / 220 (16%)
Patients (one or both sites) | 17 / 101 (17%) | 36 / 101 (36%) | 11 / 107 (10%) | 28 / 110 (25%)

In the two clinical studies above and an additional study (619 patients), the adverse effects of tooth staining or altered taste perception were not reported after the use of PerioChip.

INDICATIONS AND USAGE

PerioChip is indicated as an adjunct to scaling and root planing procedures for reduction of pocket depth in patients with adult periodontitis. PerioChip may be used as a part of a periodontal maintenance program, which includes good oral hygiene and scaling and root planing.

CONTRAINDICATIONS

PerioChip should not be used in any patient who has a known sensitivity to chlorhexidine.

PRECAUTIONS

General

The use of PerioChip in an acutely abscessed periodontal pocket has not been studied and therefore is not recommended. Although rare, infectious events including abscesses and cellulitis, which have been reported after scaling and root planing alone, have also been reported with the adjunctive placement of the PerioChip post scaling and root planing. Management of patients with periodontal disease should include consideration of potentially contributing medical disorders, such as cancer, diabetes, and immunocompromised status.

Information for Patients

Patients should avoid dental floss at the site of PerioChip insertion for 10 days after placement, because flossing might dislodge the chip. All other oral hygiene may be continued as usual. No restrictions regarding dietary habits are needed. Dislodging of the PerioChip is uncommon; however, patients should be instructed to notify the dentist promptly if the PerioChip dislodges. Patients should be also be advised that, although some mild to moderate sensitivity is normal during the first week after placement of PerioChip, they should notify the dentist promptly if pain, swelling, or other problems occur.

Carcinogenesis, Mutagenesis, Impairment of Fertility

Chlorhexidine gluconate has not been evaluated for carcinogenic potential in connection with the PerioChip. No evidence that chlorhexidine gluconate has potential to cause genetic toxicity was obtained in a battery of mutagenicity studies, including (in vitro) an Ames assay, a chromosome aberration assay in CHO cells, and (in vivo) a micronucleus assay conducted in mice.

Pregnancy

Teratogenic Effects: Pregnancy Category C – Animal reproduction studies have not been conducted in relation to PerioChip, because animal models that would permit use of a clinically relevant route of administration are not available. Chlorhexidine gluconate did not induce harm to the fetus when administered to rats by gavage at dosages up to 68.5 mg/kg/day. While chlorhexidine is known to be very poorly absorbed from the GI tract, it may be absorbed following placement within a periodontal pocket. Therefore, it is unclear whether these data are relevant to clinical use of PerioChip. In clinical studies, placement of four PerioChips within periodontal pockets resulted in plasma concentrations of chlorhexidine that were at or below the limit of detection. However, it is not known whether PerioChip can cause fetal harm when administered to a pregnant woman or can affect reproductive capacity. PerioChip should be used in a pregnant woman only if clearly needed.

Pediatric Use: The safety and effectiveness of PerioChip in pediatric patients have not been established.

Geriatric Use: Although subjects aged 65 years and over were included in clinical studies of PerioChip, there were not sufficient numbers of these subjects to determine whether they respond differently from younger subjects. Other reported clinical experience has not identified differences in responses between the elderly and younger patients. Overall differences in safety or effectiveness have not been identified between the elderly and younger patients.

ADVERSE REACTIONS

The most frequently observed adverse events in the two pivotal clinical trials were toothache, upper respiratory tract infection, and headache. Toothache was the only adverse reaction that was significantly higher (p = 0.042) in the PerioChip group when compared to placebo. Most oral pain or sensitivity occurred within the first week of the initial chip placement following SRP procedures, was mild to moderate in nature, and spontaneously resolved within days. These reactions were observed less frequently with subsequent chip placement at 3 and 6 months.

Table 3 lists adverse events, occurring in ≥ 1% of 225 patients that received PerioChip, pooled from the two pivotal clinical trials without regard to causality. Gingival bleeding was the only dental adverse event occurring at a rate of ≤ 1% in both groups.

Table 3
Adverse events (frequency ≥ 1% for the PerioChip group)
reported from 2 five-center U.S. clinical trials
 | PerioChip Total N = 225 | PerioChip Total N = 225 | PerioChip Total N = 222 | PerioChip Total N = 222
 | N | % | N | %
All patients with Adverse Events | 193 | 85.8 | 189 | 85.1
Toothache* | 114 | 50.7 | 92 | 41.4
Upper resp tract infection | 64 | 28.4 | 58 | 26.1
Headache | 61 | 27.1 | 61 | 27.5
Sinusitis | 31 | 13.8 | 29 | 13.1
Influenza-like symptoms | 17 | 7.6 | 21 | 9.5
Back pain | 15 | 6.7 | 25 | 11.3
Tooth disorder** | 14 | 6.2 | 15 | 6.8
Bronchitis | 14 | 6.2 | 7 | 3.2
Abscess | 13 | 5.8 | 13 | 5.9
Pain | 11 | 4.9 | 11 | 5.0
Allergy | 9 | 4.0 | 13 | 5.9
Myalgia | 9 | 4.0 | 9 | 4.1
Gum hyperplasia | 8 | 3.6 | 5 | 2.3
Pharyngitis | 8 | 3.6 | 5 | 2.3
Arthralgia | 7 | 3.1 | 13 | 5.9
Dysmenorrhea | 7 | 3.1 | 13 | 5.9
Dyspepsia | 7 | 3.1 | 6 | 2.7
Rhinitis | 6 | 2.7 | 11 | 5.0
Coughing | 6 | 2.7 | 7 | 3.2
Arthrosis | 6 | 2.7 | 4 | 1.8
Hypertension | 5 | 2.2 | 6 | 2.7
Stomatitis ulcerative | 5 | 2.2 | 1 | 0.5
Tendinitis | 5 | 2.2 | 1 | 0.5

* Includes dental, gingival or mouth pain, tenderness, aching, throbbing, soreness,
discomfort, or sensitivity

** Includes broken, cracked or fractured teeth, mobile teeth, and lost bridges, crowns,
or fillings

DOSAGE AND ADMINISTRATION

One PerioChip is inserted into a periodontal pocket with probing pocket depth (PD) ≥ 5 mm. Up to 8 PerioChips may be inserted in a single visit. Treatment is recommended to be administered once every three months in pockets with PD remaining ≥ 5 mm.
The periodontal pocket should be isolated and the surrounding area dried prior to chip insertion. The PerioChip should be grasped using forceps (such that the rounded end points away from the forceps) and inserted into the periodontal pocket to its maximum depth. If necessary, the PerioChip can be further maneuvered into position using the tips of the forceps or a flat instrument. The PerioChip does not need to be removed since it biodegrades completely.
In the unlikely event of PerioChip dislodgement (in the two pivotal clinical trials, only 8 chips were reported lost), several actions are recommended, depending on the day of PerioChip loss. If dislodgement occurs 7 days or more after placement, the dentist should consider the subject to have received a full course of treatment. If dislodgement occurs within 48 hours after placement, a new PerioChip should be inserted. If dislodgement occurs more than 48 hours after placement, the dentist should not replace the PerioChip, but reevaluate the patient at 3 months and insert a new PerioChip if the pocket depth has not been reduced to less than 5 mm.

HOW SUPPLIED

PerioChip (chlorhexidine gluconate) 2.5 mg is supplied as a small, orange-brown, rectangular chip (rounded at one end), in cartons of 10 chips (NDC 52096-001-12) and 20 chips (NDC 52096-001-22). Each chip is individually packed in a separate compartment of an aluminum blister pack.

Store at controlled room temperature 15° - 25°C (59° - 77°F) (see USP).

Rx only.

Instructions for Insertion

PerioChip® 2.5 mg

(chlorhexidine gluconate)

Manufactured by: DEXCEL PHARMA TECHNOLOGIES LTD., Jerusalem, Israel.

Distributed by: Adrian Pharmaceuticals, 5331 Commercial Way - Suite 211, Spring Hill, FL 34606

Tel.: 1-866-PerioChip

www.periochip.com

458-01

1269350115

Iss. 12/09

Blister Label

PerioChip® 2.5 mg

(chlorhexidine gluconate)

Store at controlled room

temperature 15°-25°C

(59°-77°F) (see USP)

Distributed by:

Adrian Pharmaceuticals

Spring Hill, FL 34606

Exp:

Batch:

Carton Label

NDC 52096-001-22 www.periochip.com 20 Chips

PerioChip®

(chlorhexidine gluconate) 2.5 mg

Store at controlled room temperature 15°-25°C (59°-77°F) (see USP).

Rx only

Manufactured by: Dexcel Pharma Technologies LTD., Jerusalem, Israel

Distributed by: Adrian Pharmaceuticals, 5331 Commercial Way - Suite 211, Spring Hill, FL 34606, Tel.: 1-866-periochip

See package insert for full prescribing information.

Barcode

3 52096 00122 2

Each PerioChip contains: chlorhexidine gluconate 2.5 mg, hydrolyzed gelatin, glutaraldehyde, glycerin, and purified water. Contains no preservatives.

Dexcel

PerioChip® 20 Chips

(chlorhexidine gluconate) 2.5 mg